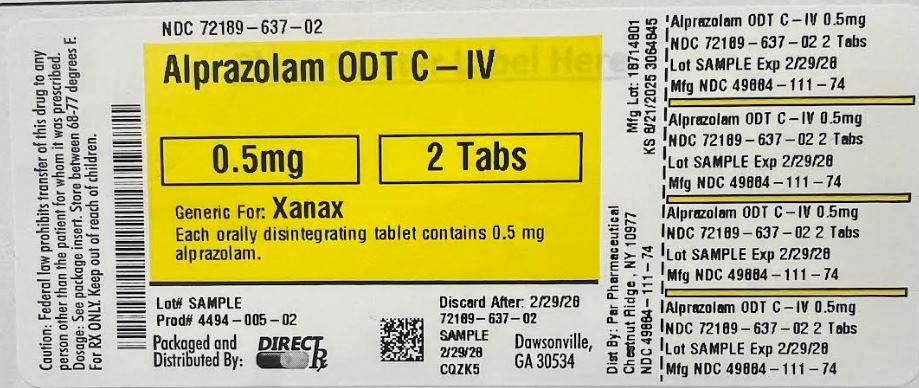 DRUG LABEL: Alprazolam ODT C-IV
NDC: 72189-637 | Form: TABLET, ORALLY DISINTEGRATING
Manufacturer: Direct_Rx
Category: prescription | Type: HUMAN PRESCRIPTION DRUG LABEL
Date: 20250822
DEA Schedule: CIV

ACTIVE INGREDIENTS: ALPRAZOLAM 0.5 mg/1 1
INACTIVE INGREDIENTS: SILICON DIOXIDE; SORBITOL; PEPPERMINT; VANILLIN; CROSPOVIDONE (15 MPA.S AT 5%); MAGNESIUM STEARATE; XYLITOL; METHACRYLIC ACID - METHYL METHACRYLATE COPOLYMER (1:1); MANNITOL; TALC; ASPARTAME

Alprazolam ODT C-IV

BOXED WARNING

WARNING: RISKS FROM CONCOMITANT USE WITH OPIOIDS; ABUSE, MISUSE, AND ADDICTION; and
DEPENDENCE AND WITHDRAWAL REACTIONS

Concomitant use of benzodiazepines and opioids may result in profound sedation, respiratory depression, coma, and death. Reserve concomitant prescribing of these drugs in patients for whom alternative treatment options are inadequate. Limit dosages and durations to the minimum required. Follow patients for signs and symptoms of respiratory depression and sedation [see Warnings and Precautions (5.1), Drug Interactions (7.1)].

The use of benzodiazepines, including Alprazolam orally disintegrating tablets, exposes users to risks of abuse, misuse, and addiction, which can lead to overdose or death. Abuse and misuse of benzodiazepines commonly involve concomitant use of other medications, alcohol, and/or illicit substances, which is associated with an increased frequency of serious adverse outcomes. Before prescribing Alprazolam orally disintegrating tablets and throughout treatment, assess each patient’s risk for abuse, misuse, and addiction [see Warnings and Precautions (5.2)].

The continued use of benzodiazepines, including Alprazolam orally disintegrating tablets, may lead to clinically significant physical dependence. The risks of dependence and withdrawal increase with longer treatment duration and higher daily dose. Abrupt discontinuation or rapid dosage reduction of Alprazolam orally disintegrating tablets after continued use may precipitate acute withdrawal reactions, which can be life-threatening. To reduce the risk of withdrawal reactions, use a gradual taper to discontinue Alprazolam orally disintegrating tablets or reduce the dosage [see Dosage and Administration (2.3) and Warnings and Precautions (5.3)].

INDICATIONS AND USAGE

1.1 Generalized Anxiety Disorder

Alprazolam orally disintegrating tablets, USP are indicated for the treatment of generalized anxiety disorder.

The efficacy of alprazolam in the treatment of generalized anxiety disorder was demonstrated in 5 short-term, placebo-controlled trials [see Clinical Studies (14.1)].

1.2 Panic Disorder

Alprazolam orally disintegrating tablets, USP are also indicated for the treatment of panic disorder, with or without agoraphobia.

The efficacy of alprazolam in the treatment of panic disorder was established in 2 short-term, placebo-controlled trials [see Clinical Studies (14.2)].

Demonstrations of the effectiveness of alprazolam by systematic clinical study are limited to 4 months in duration for generalized anxiety disorder and 4 to 10 weeks duration for panic disorder; however, patients with panic disorder have been treated on an open basis for up to 8 months without apparent loss of benefit. The physician should periodically reassess the usefulness of the drug for the individual patient.

DOSAGE AND ADMINISTRATION

Dosage should be individualized for maximum beneficial effect. While the usual daily dosages given below will meet the needs of most patients, there will be some who require doses greater than 4 mg per day. In such cases, the dosage should be increased cautiously to avoid adverse reactions. In general, benzodiazepines should be prescribed for short periods. Reevaluate the need for continued therapy before extending the treatment period.

2.1 Generalized Anxiety Disorder

Initiate treatment with a dose of 0.25 mg to 0.5 mg three times daily. The dose may be increased to achieve a maximum therapeutic effect, at intervals of 3 to 4 days, to a maximum daily dose of 4 mg, given in divided doses. Use the lowest possible effective dose, and periodically reassess the need for continued treatment. The risk of dependence can increase with dose and duration of treatment.

2.2 Panic Disorder

The successful treatment of many panic disorder patients has required the use of alprazolam at doses greater than 4 mg daily. In controlled trials conducted to establish the efficacy of alprazolam in panic disorder, doses in the range of 1 mg to 10 mg daily were used. The mean dosage employed was approximately 5 mg to 6 mg daily. Among the approximately 1700 patients participating in the panic disorder development program, about 300 received alprazolam in dosages of greater than 7 mg per day, including approximately 100 patients who received maximum dosages of greater than 9 mg per day. Occasional patients required as much as 10 mg a day to achieve a successful response.

Dose Titration

Initiate treatment with a dose of 0.5 mg three times daily. Depending on the response, the dose may be increased at intervals of 3 to 4 days in increments of no more than 1 mg per day. Slower titration to the dose levels greater than 4 mg per day may be advisable to allow full expression of the pharmacodynamic effect of alprazolam. To lessen the possibility of interdose symptoms, the times of administration should be distributed as evenly as possible throughout the waking hours, (i.e., administered three or four times daily).

Generally, therapy should be initiated at a low dose to minimize the risk of adverse responses in patients especially sensitive to the drug. The dose should be advanced until an acceptable therapeutic response (i.e., a substantial reduction in or total elimination of panic attacks) is achieved, intolerance occurs, or the maximum recommended dose is attained.

Dose Maintenance

For patients receiving doses greater than 4 mg per day, periodically reassess treatment and consider a reduction of dosage. In a controlled postmarketing dose-response study, patients treated with doses of alprazolam greater than 4 mg per day for 3 months were able to taper to 50% of their total daily maintenance dose without apparent loss of clinical benefit. Because of the danger of withdrawal, avoid abrupt discontinuation of treatment [see Warnings and Precautions (5.3), Drug Abuse and Dependence (9.3)].

The necessary duration of treatment for panic disorder patients responding to alprazolam is unknown. After a period of extended freedom from attacks, a carefully supervised tapered discontinuation may be attempted, but there is evidence that this may often be difficult to accomplish without recurrence of symptoms and/or the manifestation of withdrawal phenomena.

2.3 Discontinuation or Dosage Reduction of Alprazolam Orally Disintegrating Tablets

To reduce the risk of withdrawal reactions, use a gradual taper to discontinue Alprazolam orally disintegrating tablets or reduce the dosage. If a patient develops withdrawal reactions, consider pausing the taper or increasing the dosage to the previous tapered dosage level. Subsequently decrease the dosage more slowly [see Warnings and Precautions (5.3) and Drug Abuse and Dependence (9.3)].

In a controlled postmarketing discontinuation study of panic disorder patients which compared this recommended taper schedule with a slower taper schedule, there was no difference between the groups in the proportion of patients who tapered and completely discontinued treatment with alprazolam; however, the slower schedule was associated with a reduction in symptoms associated with a withdrawal syndrome. Reduce the dose by no more than 0.5 mg every 3 days. Some patients may benefit from an even more gradual discontinuation. Some patients may prove resistant to all discontinuation regimens.

2.4 Dosing in Special Populations

In elderly patients, in patients with advanced liver disease, or in patients with debilitating disease (e.g., severe pulmonary disease), the usual starting dose is 0.25 mg, given two or three times daily. This may be gradually increased if needed and tolerated. The elderly may be especially sensitive to the effects of benzodiazepines. If adverse reactions occur at the recommended starting dose, the dose may be lowered.

2.5 Instructions to be Given to Patients for Use/Handling Alprazolam Orally Disintegrating Tablets

Just prior to administration, with dry hands, remove the tablet from the blister. Immediately place the alprazolam orally disintegrating tablet on top of the tongue where it will disintegrate and be swallowed with saliva. Administration with liquid is not necessary.

DOSAGE FORMS AND STRENGTHS

0.25 mg, 0.5 mg, 1.0 mg, and 2.0 mg scored orally disintegrating tablets, USP.

CONTRAINDICATIONS

Alprazolam orally disintegrating tablets are contraindicated in patients with acute narrow angle glaucoma. Alprazolam orally disintegrating tablets can exacerbate narrow angle closure. Alprazolam orally disintegrating tablets may be used in patients with open angle glaucoma who are receiving appropriate therapy.

Alprazolam orally disintegrating tablets are contraindicated in patients treated with potent CYP3A4 inhibitors (e.g., ketoconazole and itraconazole), because these medications significantly impair the oxidative metabolism mediated by cytochrome P450 3A (CYP3A) and can increase alprazolam exposures [see Clinical Pharmacology (12.3), Warnings and Precautions (5.9), and Drug Interactions (7.4)].

WARNINGS AND PRECAUTIONS

5.1 Risks from Concomitant Use with Opioids

Concomitant use of benzodiazepines, including alprazolam, and opioids may result in profound sedation, respiratory depression, coma, and death. Because of these risks, reserve concomitant prescribing of these drugs in patients for whom alternative treatment options are inadequate.

Observational studies have demonstrated that concomitant use of opioid analgesics and benzodiazepines increases the risk of drug-related mortality compared to use of opioids alone. If a decision is made to prescribe alprazolam concomitantly with opioids, prescribe the lowest effective dosages and minimum durations of concomitant use, and follow patients closely for signs and symptoms of respiratory depression and sedation. In patients already receiving an opioid analgesic, prescribe a lower initial dose of alprazolam than indicated in the absence of an opioid and titrate based on clinical response. If an opioid is initiated in a patient already taking alprazolam, prescribe a lower initial dose of the opioid and titrate based upon clinical response.

Advise both patients and caregivers about the risks of respiratory depression and sedation when alprazolam is used with opioids. Advise patients not to drive or operate heavy machinery until the effects of concomitant use with the opioid have been determined [see Drug Interactions (7.1)].

5.2 Abuse, Misuse, and Addiction

The use of benzodiazepines, including Alprazolam orally disintegrating tablets, exposes users to the risks of abuse, misuse, and addiction, which can lead to overdose or death. Abuse and misuse of benzodiazepines often (but not always) involve the use of doses greater than the maximum recommended dosage and commonly involve concomitant use of other medications, alcohol, and/or illicit substances, which is associated with an increased frequency of serious adverse outcomes, including respiratory depression, overdose, or death [see Drug Abuse and Dependence (9.2)].

Before prescribing Alprazolam orally disintegrating tablets and throughout treatment, assess each patient’s risk for abuse, misuse, and addiction (e.g., using a standardized screening tool). Use of alprazolam orally disintegrating tablets, particularly in patients at elevated risk, necessitates counseling about the risks and proper use of alprazolam orally disintegrating tablets along with monitoring for signs and symptoms of abuse, misuse, and addiction. Prescribe the lowest effective dosage; avoid or minimize concomitant use of CNS depressants and other substances associated with abuse, misuse, and addiction (e.g., opioid analgesics, stimulants); and advise patients on the proper disposal of unused drug. If a substance use disorder is suspected, evaluate the patient and institute (or refer them for) early treatment, as appropriate.

5.3 Dependence and Withdrawal Reactions

To reduce the risk of withdrawal reactions, use a gradual taper to discontinue Alprazolam orally disintegrating tablets or reduce the dosage (a patient-specific plan should be used to taper the dose) [see Dosage and Administration (2.3)].

Patients at an increased risk of withdrawal adverse reactions after benzodiazepine discontinuation or rapid dosage reduction include those who take higher dosages, and those who have had longer durations of use.

Acute Withdrawal Reactions

The continued use of benzodiazepines, including Alprazolam orally disintegrating tablets, lead to clinically significant physical dependence. Abrupt discontinuation or rapid dosage reduction of Alprazolam orally disintegrating tablets after continued use, or administration of flumazenil (a benzodiazepine antagonist) may precipitate acute withdrawal reactions, which can be life-threatening (e.g., seizures) [see Drug Abuse and Dependence (9.3)].

Protracted Withdrawal Syndrome

In some cases, benzodiazepine users have developed a protracted withdrawal syndrome with withdrawal symptoms lasting weeks to more than 12 months [see Drug Abuse and Dependence (9.3)].

Certain adverse clinical events, some life-threatening, are a direct consequence of physical dependence to alprazolam. These include a spectrum of withdrawal symptoms; the most important is seizure [see Drug Abuse and Dependence (9.3)]. Spontaneous reporting system data suggest that the risk of dependence and its severity appear to be greater in patients treated with doses greater than 4 mg per day and for long periods (more than 12 weeks). However, in a controlled postmarketing discontinuation study of panic disorder patients, the duration of treatment (3 months compared to 6 months) had no effect on the ability of patients to taper to zero dose. In contrast, patients treated with doses of alprazolam greater than 4 mg per day had more difficulty tapering to zero dose than those treated with less than 4 mg per day.

The importance of dose and the risks of Alprazolam as a treatment for panic disorder

Because the management of panic disorder often requires the use of average daily doses of alprazolam above 4 mg, the risk of dependence among panic disorder patients may be higher than that among those treated for less severe anxiety. Experience in randomized placebo-controlled discontinuation studies of patients with panic disorder showed a high rate of rebound and withdrawal symptoms in patients treated with alprazolam compared to placebo-treated patients.

Relapse or return of illness was defined as a return of symptoms characteristic of panic disorder (primarily panic attacks) to levels approximately equal to those seen at baseline before active treatment was initiated. Rebound refers to a return of symptoms of panic disorder to a level substantially greater in frequency, or more severe in intensity than seen at baseline. Withdrawal symptoms were identified as those which were generally not characteristic of panic disorder and which occurred for the first time more frequently during discontinuation than at baseline.

In a controlled clinical trial in which 63 patients were randomized to alprazolam and where withdrawal symptoms were specifically sought, the following were identified as symptoms of withdrawal: heightened sensory perception, impaired concentration, dysosmia, clouded sensorium, paresthesias, muscle cramps, muscle twitch, diarrhea, blurred vision, appetite decrease, and weight loss. Other symptoms, such as anxiety and insomnia, were frequently seen during discontinuation, but it could not be determined if they were due to return of illness, rebound, or withdrawal.

In two controlled trials of 6 to 8 weeks duration where the ability of patients to discontinue medication was measured, 71% to 93% of patients treated with alprazolam tapered completely off therapy compared to 89% to 96% of placebo-treated patients. In a controlled postmarketing discontinuation study of panic disorder patients, the duration of treatment (3 months compared to 6 months) had no effect on the ability of patients to taper to zero dose.

Seizures attributable to alprazolam were seen after drug discontinuance or dose reduction in 8 of 1980 patients with panic disorder or in patients participating in clinical trials where doses of alprazolam greater than 4 mg/day for over 3 months were permitted. Five of these cases clearly occurred during abrupt dose reduction, or discontinuation from daily doses of 2 mg to 10 mg. Three cases occurred in situations where there was not a clear relationship to abrupt dose reduction or discontinuation. In one instance, seizure occurred after discontinuation from a single dose of 1 mg after tapering at a rate of 1 mg every 3 days from 6 mg daily. In two other instances, the relationship to taper is indeterminate; in both of these cases the patients had been receiving doses of 3 mg daily prior to seizure. The duration of use in the above 8 cases ranged from 4 to 22 weeks. There have been occasional voluntary reports of patients developing seizures while apparently tapering gradually from alprazolam. The risk of seizure seems to be greatest 24 to 72 hours after discontinuation [see Dosage and Administration (2)].

To discontinue treatment in patients taking alprazolam, the dosage should be reduced gradually. Decrease the daily dosage of alprazolam by no more than 0.5 mg every three days [see Dosage and Administration (2.3)]. Some patients may benefit from an even slower dosage reduction. In a controlled postmarketing discontinuation study of panic disorder patients which compared this recommended taper schedule with a slower taper schedule, no difference was observed between the groups in the proportion of patients who tapered to zero dose; however, the slower schedule was associated with a reduction in symptoms associated with a withdrawal syndrome.

5.4 Suicide and Overdose

As with other psychotropic medications, the usual precautions with respect to administration of the drug and size of the prescription are indicated for severely depressed patients or those in whom there is reason to expect concealed suicidal ideation or plans. Panic disorder has been associated with primary and secondary major depressive disorders and increased reports of suicide among untreated patients.

5.5 Status Epilepticus

Withdrawal seizures have been reported in association with the discontinuation of alprazolam. In most cases, only a single seizure was reported; however, multiple seizures and status epilepticus were reported as well.

5.6 CNS Depression and Impaired Performance

Because alprazolam has CNS depressant effects and has the potential to impair judgment, cognition, and motor performance, caution patients against engaging in hazardous occupations or activities requiring complete mental alertness such as operating machinery or driving a motor vehicle, until they are reasonably certain that alprazolam treatment does not affect them adversely. Caution patients about the simultaneous ingestion of alcohol and other CNS depressant drugs during treatment with alprazolam.

5.7 Mania

Episodes of hypomania and mania have been reported in association with the use of alprazolam in patients with depression.

5.8 Neonatal Sedation and Withdrawal Syndrome

Use of alprazolam late in pregnancy can result in sedation (respiratory depression, lethargy, hypotonia) and/or withdrawal symptoms (hyperreflexia, irritability, restlessness, tremors, inconsolable crying, and feeding difficulties) in the neonate [see Use in Specific Populations (8.1)]. Monitor neonates exposed to Alprazolam orally disintegrating tablets during pregnancy or labor for signs of sedation and monitor neonates exposed to Alprazolam orally disintegrating tablets during pregnancy for signs of withdrawal; manage these neonates accordingly.

5.9 Alprazolam Interaction with Drugs that Inhibit Metabolism via Cytochrome P450 3A

The initial step in alprazolam metabolism is hydroxylation catalyzed by cytochrome P450 3A (CYP3A). Drugs that inhibit this metabolic pathway may have a profound effect on the clearance of alprazolam. Consequently, alprazolam should be avoided in patients receiving potent inhibitors of CYP3A. With drugs inhibiting CYP3A to a lesser but still significant degree, alprazolam should be used only with caution and consideration of appropriate dosage reduction. For some drugs, an interaction with alprazolam has been quantified with clinical data; for other drugs, interactions are predicted from in vitro data and/or experience with similar drugs in the same pharmacologic class.

The following are examples of drugs known to inhibit the metabolism of alprazolam and/or related benzodiazepines, presumably through inhibition of CYP3A.

Potent CYP3A Inhibitors

Azole antifungal agents— Ketoconazole and itraconazole are potent CYP3A inhibitors and have been shown in vivo to increase plasma alprazolam concentrations 3.98 fold and 2.70 fold, respectively. The coadministration of alprazolam with these agents is not recommended. Other azole-type antifungal agents should also be considered potent CYP3A inhibitors and the coadministration of alprazolam with them is not recommended [see CONTRAINDICATIONS (4)].

Drugs demonstrated to be CYP3A inhibitors on the basis of clinical studies involving alprazolam

Consider dose reduction of alprazolam during coadministration with the following drugs:

Nefazodone — Coadministration of nefazodone increased alprazolam concentration two-fold.
Fluvoxamine — Coadministration of fluvoxamine approximately doubled the maximum plasma concentration of alprazolam, decreased clearance by 49%, increased half-life by 71%, and decreased measured psychomotor performance.
Cimetidine — Coadministration of cimetidine increased the maximum plasma concentration of alprazolam by 86%, decreased clearance by 42%, and increased half-life by 16%.

Other drugs possibly affecting alprazolam metabolism

Other drugs possibly affect alprazolam metabolism by inhibition of CYP3A [see Drug Interactions (7.6)].

5.10 Interdose Symptoms

Early morning anxiety and emergence of anxiety symptoms between doses of alprazolam have been reported in patients with panic disorder taking prescribed maintenance doses of alprazolam. These symptoms may reflect the development of tolerance or a time interval between doses which is longer than the duration of clinical action of the administered dose. In either case, it is presumed that the prescribed dose is not sufficient to maintain plasma levels above those needed to prevent relapse, rebound or withdrawal symptoms over the entire course of the interdosing interval. In these situations, it is recommended that the same total daily dose be given divided as more frequent administrations [see Dosage and Administration (2)].

5.11 Uricosuric Effect

Alprazolam has a weak uricosuric effect. Although other medications with weak uricosuric effect have been reported to cause acute renal failure, there have been no reported instances of acute renal failure attributable to therapy with alprazolam.

5.12 Use in Patients with Concomitant Illness

It is recommended that the dosage be limited to the smallest effective dose to preclude the development of ataxia or oversedation which may be a particular problem in elderly or debilitated patients [see Dosage and Administration (2)]. The usual precautions in treating patients with impaired renal, hepatic or pulmonary function should be observed. There have been rare reports of death in patients with severe pulmonary disease shortly after the initiation of treatment with alprazolam. A decreased systemic alprazolam elimination rate (e.g., increased plasma half-life) has been observed in both alcoholic liver disease patients and obese patients receiving alprazolam [see Clinical Pharmacology (12)].

5.13 Risks in Patients with Phenylketonuria

Phenylketonuric patients should be informed that alprazolam orally disintegrating tablets contain phenylalanine (a component of aspartame). Each 0.25 mg, 0.5 mg, 1 mg and 2 mg orally disintegrating tablet contains 2.52 mg, 5.04 mg, 5.04 mg and 10.08 mg of phenylalanine, respectively [see Description (11.1)].

ADVERSE REACTIONS

6.1 Clinical Trial Experience

The most commonly reported (greater than or equal to 5% and ~ twice the rate of placebo) adverse reactions with alprazolam treatment are: sedation, impaired coordination, dysarthria, and increased libido.

The data cited in the two tables below are estimates of adverse reactions occurring in patients who participated in clinical trials under the following conditions: relatively short duration (four weeks) placebo-controlled clinical studies with dosages up to 4 mg per day of alprazolam (for the management of anxiety disorders or for the short-term relief of the symptoms of anxiety) and short-term (up to ten weeks) placebo-controlled clinical studies with dosages up to 10 mg per day of alprazolam in patients with panic disorder, with or without agoraphobia.

Because clinical trials are conducted under widely varying conditions, adverse reaction rates observed in the clinical trials of a drug cannot be directly compared to rates in the clinical trials of another drug and may not reflect the rates observed in practice.

Comparison of the cited figures, however, can provide the prescriber with some basis for estimating the relative contributions of drug and non-drug factors to the adverse reaction incidence in the population studied. Even this use must be approached cautiously, as a drug may relieve a symptom in one patient but induce it in others. (For example, an anxiolytic drug may relieve dry mouth [a symptom of anxiety] in some subjects but induce dry mouth in others.)

Table 1: Adverse Reactions Reported in Placebo-Controlled Trials of Alprazolam in Generalized Anxiety Disorder (>2% and at a rate greater than placebo)
GENERALIZED ANXIETY DISORDER

Body System/Adverse Reaction

Treatment-Emergent Symptom Incidencea

ALPRAZOLAM (%)

N=565

PLACEBO (%)

N=505

Central Nervous System

Sedation

41

22

Lightheadedness

21

19

Dizziness

2

1

Akathisia

2

1

Gastrointestinal

Dry Mouth

15

13

Increased Salivation

4

2

Cardiovascular

Hypotension

5

2

Cutaneous

Dermatitis/Allergy

4

3

aEvents reported by 1% or more of alprazolam patients are included.

In addition to the relatively common (i.e., greater than 1%) adverse reactions described in the table above, the following adverse reactions have been reported in association with the use of benzodiazepines: dystonia, irritability, concentration difficulties, anorexia, transient amnesia or memory impairment, loss of coordination, fatigue, seizures, sedation, slurred speech, jaundice, musculoskeletal weakness, pruritus, diplopia, dysarthria, changes in libido, menstrual irregularities, incontinence and urinary retention.

Table 2: Adverse Reactions Reported in Placebo-Controlled Trials of Alprazolam in Panic Disorder (>2 % and greater than placebo)
PANIC DISORDER
Body System/Adverse Reaction Treatment-Emergent Symptom Incidencea

Central Nervous System

ALPRAZOLAM (%)

N=1388

PLACEBO (%)

N=1231

Sedation

77

43

Fatigue and Tiredness

49

42

Impaired Coordination

40

18

Irritability

33

30

Memory Impairment

33

22

Cognitive Disorder

29

21

Dysarthria

23

6

Decreased Libido

14

8

Confusional State

10

8

Increased Libido

8

4

Change in Libido (Not Specified)

7

6

Disinhibition

3

2

Talkativeness

2

1

Derealization

2

1

Gastrointestinal

Constipation

26

15

Increased Salivation

6

4

Cutaneous

Rash

11

8

Other

Increased Appetite

33

23

Decreased Appetite

28

24

Weight Gain

27

18

Weight Loss

23

17

Micturition Difficulties

12

9

Menstrual Disorders

10

9

Sexual Dysfunction

7

4

Incontinence

2

1

aEvents reported by 1% or more of alprazolam patients are included.

In addition to the relatively common (i.e., greater than 1%) adverse reactions described in the table above, the following adverse reactions have been reported in association with the use of alprazolam: seizures, hallucinations, depersonalization, taste alterations, diplopia, elevated bilirubin, elevated hepatic enzymes, and jaundice.

Panic disorder has been associated with primary and secondary major depressive disorders and increased reports of suicide among untreated patients [see Warnings and Precautions (5.4)].

6.2 Postmarketing Experience

The following adverse reactions have been identified during postmarketing use of alprazolam. Because these reactions are reported voluntarily from a population of uncertain size, it is not always possible to reliably estimate their frequency or establish a causal relationship to drug exposure. Reported events include: liver enzyme elevations, hepatitis, hepatic failure, Stevens-Johnson syndrome, hyperprolactinemia, gynecomastia, and galactorrhea.

DRUG INTERACTIONS

7.1 Use with Other CNS Depressants

The concomitant use of benzodiazepines and opioids increases the risk of respiratory depression because of actions at different receptor sites in the CNS that control respiration. Benzodiazepines interact at GABAA sites and opioids interact primarily at mu receptors. When benzodiazepines and opioids are combined, the potential for benzodiazepines to significantly worsen opioid-related respiratory depression exists. Limit dosage and duration of concomitant use of benzodiazepines and opioids, and monitor patients closely for respiratory depression and sedation.

If alprazolam orally disintegrating tablets are coadministered with other psychotropic agents or anticonvulsant drugs, carefully consider the pharmacology of the agents to be employed, particularly with compounds which might potentiate the action of benzodiazepines. The benzodiazepines, including alprazolam, produce additive CNS depressant effects when coadministered with other psychotropic medications, anticonvulsants, antihistaminics, alcohol and other drugs which themselves produce CNS depression.

7.2 Drugs Effecting Salivary Flow and Stomach pH

Because alprazolam orally disintegrating tablets disintegrate in the presence of saliva, and the formulation requires an acidic environment to dissolve, concomitant drugs or diseases that cause dry mouth or raise stomach pH might slow disintegration or dissolution, resulting in slowed or decreased absorption.

7.3 Use with Imipramine and Desipramine

The steady state plasma concentrations of imipramine and desipramine can increase by approximately 30% and 20%, respectively, when administered concomitantly with alprazolam in doses up to 4 mg per day. The clinical significance of these changes is unknown.

7.4 Drugs that Inhibit Alprazolam Metabolism via Cytochrome P450 3A

The initial step in alprazolam metabolism is hydroxylation catalyzed by cytochrome P450 3A (CYP3A). Drugs which inhibit this metabolic pathway can have a profound effect on the clearance of alprazolam [see Contraindications (4) and Warnings and Precautions (5.8)].

7.5 Drugs Demonstrated to be CYP3A Inhibitors of Possible Clinical Significance on the Basis of Clinical Studies Involving Alprazolam

Use caution during coadministration of Alprazolam and the following drugs:

Fluoxetine — Coadministration of fluoxetine with alprazolam increased the maximum plasma concentration of alprazolam by 46%, decreased clearance by 21%, increased half-life by 17%, and decreased measured psychomotor performance.

Propoxyphene — Coadministration of propoxyphene decreased the maximum plasma concentration of alprazolam by 6%, decreased clearance by 38%, and increased half-life by 58%.

Oral Contraceptives — Coadministration of oral contraceptives increased the maximum plasma concentration of alprazolam by 18%, decreased clearance by 22%, and increased half-life by 29%.

7.6 Drugs and Other Substances Demonstrated to be CYP3A Inhibitors on the Basis of Clinical Studies Involving Benzodiazepines Metabolized Similarly to Alprazolam or on the Basis of In Vitro Studies with Alprazolam or Other Benzodiazepines

Use caution during the coadministration of Alprazolam and the following:

Available data from clinical studies of benzodiazepines other than alprazolam suggest a possible drug interaction between alprazolam and the following: diltiazem, isoniazid, macrolide antibiotics such as erythromycin and clarithromycin, and grapefruit juice. Data from in vitro studies of alprazolam suggest a possible drug interaction between alprazolam and the following: sertraline and paroxetine. However, data from an in vivo drug interaction study involving a single dose of alprazolam 1 mg and steady state doses of sertraline (50 mg to 150 mg per day) did not reveal any clinically significant changes in the pharmacokinetics of alprazolam. Data from in vitro studies of benzodiazepines other than alprazolam suggest a possible drug interaction between benzodiazepines and the following: ergotamine, cyclosporine, amiodarone, nicardipine, and nifedipine [see Warnings and Precautions (5.8)].

7.7 Inducers of CYP3A

Carbamazepine can increase alprazolam metabolism and therefore can decrease plasma levels of alprazolam.

USE IN SPECIFIC POPULATIONS

8.1 Pregnancy

Pregnancy Exposure Registry

There is a pregnancy exposure registry that monitors pregnancy outcomes in women exposed to psychiatric medication, including Alprazolam orally disintegrating tablets, during pregnancy. Healthcare providers are encouraged to register patients by calling the National Pregnancy Registry for Psychiatric Medications at 1-866-961-2388 or visiting online at https://womensmentalhealth.org/pregnancyregistry/.

Risk Summary

Neonates born to mothers using benzodiazepines late stages in pregnancy have been reported to experience symptoms of sedation and/or neonatal withdrawal [see Warnings and Precautions (5.8) and Clinical Considerations)]. Available data from published observational studies of pregnant women exposed to benzodiazepines do not report a clear drug association with benzodiazepines and major birth defects (see Data).

The background risk of major birth defects and miscarriage for the indicated population is unknown. All pregnancies have a background risk of birth defect, loss, or other adverse outcomes. In the U.S. general population, the estimated risk of major birth defects and of miscarriage in clinically recognized pregnancies is 2% to 4% and 15% to 20%, respectively.

Clinical Considerations

Fetal/Neonatal adverse reactions

Benzodiazepines cross the placenta and may produce respiratory depression, and sedation in neonates. Monitor neonates exposed to alprazolam during pregnancy or labor for signs of sedation, respiratory depression, hypotonia, and feeding problems. Monitor neonates exposed to alprazolam during pregnancy for signs of withdrawal. Manage these neonates accordingly [see Warnings and Precautions (5.8)].

Data

Human Data

Published data from observational studies on the use of benzodiazepines during pregnancy do not report a clear association with benzodiazepines and major birth defects. Although early studies reported an increased risk of congenital malformations with diazepam and chlordiazepoxide, there was no consistent pattern noted. In addition, the majority of recent case-control and cohort studies of benzodiazepine use during pregnancy, which were adjusted for confounding exposures to alcohol, tobacco, and other medications, have not confirmed these findings.

8.2 Lactation

Risk Summary

Limited data from published literature reports the presence of alprazolam in human breast milk. There are reports of sedation, poor feeding and poor weight gain in infants exposed to benzodiazepines through breast milk. The effects of alprazolam on lactation are unknown.

Because of the potential for serious adverse reactions, including sedation and withdrawal symptoms in breastfed infants, advise patients that breastfeeding is not recommended during treatment with Alprazolam orally disintegrating tablets.

8.4 Pediatric Use

Safety and effectiveness of alprazolam in individuals below 18 years of age have not been studied.

8.5 Geriatric Use

The elderly may be more sensitive to the effects of benzodiazepines. They exhibit higher plasma alprazolam concentrations due to reduced clearance of the drug, compared with a younger population receiving the same doses. The smallest effective dose of alprazolam should be used in the elderly to preclude the development of ataxia and oversedation [see Clinical Pharmacology (12) and Dosage and Administration (2)].

Changes in the absorption, distribution, metabolism and excretion of benzodiazepines have been demonstrated in geriatric patients. A mean half-life of alprazolam of 16.3 hours has been observed in healthy elderly subjects (range: 9.0 to 26.9 hours, n=16) compared to 11.0 hours (range: 6.3 to 15.8 hours, n=16) in healthy adult subjects.

DRUG ABUSE AND DEPENDENCE

9.1 Controlled Substance

Alprazolam is a Schedule IV controlled substance.

9.2 Abuse

Alprazolam orally disintegrating tablet is a benzodiazepine and a CNS depressant with a potential for abuse and addiction. Abuse is the intentional, non-therapeutic use of a drug, even once, for its desirable psychological or physiological effects. Misuse is the intentional use, for therapeutic purposes, of a drug by an individual in a way other than prescribed by a health care provider or for whom it was not prescribed. Drug addiction is a cluster of behavioral, cognitive, and physiological phenomena that may include a strong desire to take the drug, difficulties in controlling drug use (e.g., continuing drug use despite harmful consequences, giving a higher priority to drug use than other activities and obligations), and possible tolerance or physical dependence. Even taking benzodiazepines as prescribed may put patients at risk for abuse and misuse of their medication. Abuse and misuse may lead to addiction.

Abuse and misuse of benzodiazepines often (but not always) involve the use of doses greater than the maximum recommended dosage and commonly involve concomitant use of other medications, alcohol, and/or illicit substances, which is associated with an increased frequency of serious adverse outcomes, including respiratory depression, overdose, or death. Benzodiazepines are often sought by individuals who abuse drugs and other substances, and by individuals with addictive disorders [see Warnings and Precautions (5.2)].

The following adverse reactions have occurred with benzodiazepine abuse and/or misuse: abdominal pain, amnesia, anorexia, anxiety, aggression, ataxia, blurred vision, confusion, depression, disinhibition, disorientation, dizziness, euphoria, impaired concentration and memory, indigestion, irritability, muscle pain, slurred speech, tremors, and vertigo.

The following severe adverse reactions have occurred with benzodiazepine abuse and/or misuse: delirium, paranoia suicidal ideation and behavior, seizures, coma, breathing difficulty, and death. Death is more often associated with polysubstance use (especially benzodiazepines with other CNS depressants such as opioids and alcohol).

9.3 Dependence

Physical Dependence

Alprazolam orally disintegrating tablets may produce physical dependence from continued therapy. Physical dependence is a state that develops as a result of physiological adaptation in response to repeated drug use, manifested by withdrawal signs and symptoms after abrupt discontinuation or a significant dose reduction of a drug. Abrupt discontinuation or rapid dosage reduction of benzodiazepines or administration of flumazenil, a benzodiazepine antagonist, may precipitate acute withdrawal reactions, including seizures, which can be life-threatening. Patients at an increased risk of withdrawal adverse reactions after benzodiazepine discontinuation or rapid dosage reduction include those who take higher dosages (i.e., higher and/or more frequent doses) and those who have had longer durations of use [see Warnings and Precautions (5.3)].

To reduce the risk of withdrawal reactions, use a gradual taper to discontinue alprazolam orally disintegrating tablets or reduce the dosage [see Dosage and Administration (2.3) and Warnings and Precautions (5.3)].

Acute Withdrawal Signs and Symptoms

Acute withdrawal signs and symptoms associated with benzodiazepines have included abnormal involuntary movements, anxiety, blurred vision, depersonalization, depression, derealization, dizziness, fatigue, gastrointestinal adverse reactions (e.g., nausea, vomiting, diarrhea, weight loss, decreased appetite), headache, hyperacusis, hypertension, irritability, insomnia, memory impairment, muscle pain and stiffness, panic attacks, photophobia, restlessness, tachycardia, and tremor. More severe acute withdrawal signs and symptoms, including life-threatening reactions, have included catatonia, convulsions, delirium tremens, depression, hallucinations, mania, psychosis, seizures, and suicidality.

Protracted Withdrawal Syndrome

Protracted withdrawal syndrome associated with benzodiazepines is characterized by anxiety, cognitive impairment, depression, insomnia, formication, motor symptoms (e.g., weakness, tremor, muscle twitches), paresthesia, and tinnitus that persists beyond 4 to 6 weeks after initial benzodiazepine withdrawal. Protracted withdrawal symptoms may last weeks to more than 12 months. As a result, there may be difficulty in differentiating withdrawal symptoms from potential re-emergence or continuation of symptoms for which the benzodiazepine was being used.

Tolerance

Tolerance to alprazolam orally disintegrating tablets may develop from continued therapy. Tolerance is a physiological state characterized by a reduced response to a drug after repeated administration (i.e., a higher dose of a drug is required to produce the same effect that was once obtained at a lower dose). Tolerance to the therapeutic effect of alprazolam orally disintegrating tablets may develop; however, little tolerance develops to the amnestic reactions and other cognitive impairments caused by benzodiazepines.

OVERDOSAGE

Overdosage of benzodiazepines is characterized by central nervous system depression ranging from drowsiness to coma. In mild to moderate cases, symptoms can include drowsiness, confusion, dysarthria, lethargy, hypnotic state, diminished reflexes, ataxia, and hypotonia. Rarely, paradoxical or disinhibitory reactions (including agitation, irritability, impulsivity, violent behavior, confusion, restlessness, excitement, and talkativeness) may occur. In severe overdosage cases, patients may develop respiratory depression and coma. Overdosage of benzodiazepines in combination with other CNS depressants (including alcohol and opioids) may be fatal [see Warnings and Precautions (5.2)]. Markedly abnormal (lowered or elevated) blood pressure, heart rate, or respiratory rate raise the concern that additional drugs and/or alcohol are involved in the overdosage.

In managing benzodiazepine overdosage, employ general supportive measures, including intravenous fluids and airway management. Flumazenil, a specific benzodiazepine receptor antagonist indicated for the complete or partial reversal of the sedative effects of benzodiazepines in the management of benzodiazepine overdosage, can lead to withdrawal and adverse reactions, including seizures, particularly in the context of mixed overdosage with drugs that increase seizure risk (e.g., tricyclic and tetracyclic antidepressants) and in patients with long-term benzodiazepine use and physical dependency. The risk of withdrawal seizures with flumazenil use may be increased in patients with epilepsy. Flumazenil is contraindicated in patients who have received a benzodiazepine for control of a potentially life-threatening condition (e.g., status epilepticus). If the decision is made to use flumazenil, it should be used as an adjunct to, not as a substitute for, supportive management of benzodiazepine overdosage. See the flumazenil injection Prescribing Information.

Consider contacting a poison center (1-800-222-1222), poisoncontrol.org, or medical toxicologist for additional overdosage management recommendations.

DESCRIPTION

Alprazolam orally disintegrating tablets, USP contain alprazolam, USP which is a triazolo analog of the 1,4 benzodiazepine class of central nervous system-active compounds.

Alprazolam orally disintegrating tablets, USP are an orally administered formulation of alprazolam, USP which rapidly disintegrates on the tongue and does not require water to aid dissolution or swallowing.

The chemical name of alprazolam, USP is 8-Chloro-1-methyl-6-phenyl-4H-s-triazolo [4,3-α] [1,4] benzodiazepine. The molecular formula is C17H13CIN4 and the molecular weight is 308.76.

The structural formula is:

[this is the structure]

Alprazolam, USP is a white crystalline powder, which is soluble in methanol or ethanol but which has no appreciable solubility in water at physiological pH.

11.1 Alprazolam Orally Disintegrating Tablets

Each orally disintegrating tablet contains either 0.25 mg, 0.5 mg, 1 mg, or 2 mg of alprazolam, USP and the following inactive ingredients: aspartame, crospovidone, basic butylated methacrylate copolymer, magnesium stearate, mannitol, silicon dioxide, sorbitol, talc, xylitol, natural peppermint flavor, artificial vanillin flavor.

CLINICAL PHARMACOLOGY

12.1 Mechanism of Action

The exact mechanism of action of alprazolam is unknown. Benzodiazepines bind to gamma aminobutyric acid (GABA) receptors in the brain and enhance GABA-mediated synaptic inhibition; such actions may be responsible for the efficacy of alprazolam in anxiety disorder and panic disorder.

12.3 Pharmacokinetics

Absorption

Following oral administration, alprazolam is readily absorbed. The peak plasma concentration is reached about 1.5 to 2 hours after administration of alprazolam given with or without water. When taken with water, mean Tmax occurs about 15 minutes earlier than when taken without water with no change in Cmax or AUC. Plasma levels are proportional to the dose given; over the dose range of 0.5 mg to 3 mg, peak levels of 8 to 37 ng/mL are observed. The elimination half-life of alprazolam is approximately 12.5 hours (range 7.9 to 19.2 hours) after administration of alprazolam in healthy adults.

Food decreased the mean Cmax by about 25% and increased the mean Tmax by 2 hours from 2.2 hours to 4.4 hours after the ingestion of a high-fat meal. Food did not affect the extent of absorption (AUC) or the elimination half-life.

Distribution

In vitro, alprazolam is bound (80 percent) to human serum protein. Serum albumin accounts for the majority of the binding.

Metabolism/Elimination

Alprazolam is extensively metabolized in humans, primarily by cytochrome P450 3A4 (CYP3A4), to two major metabolites in the plasma: 4-hydroxyalprazolam and α-hydroxyalprazolam. A benzophenone derived from alprazolam is also found in humans. Their half-lives appear to be similar to that of alprazolam. The plasma concentrations of 4-hydroxyalprazolam and α-hydroxyalprazolam relative to unchanged alprazolam concentration were always less than 4%. The reported relative potencies in benzodiazepine receptor binding experiments and in animal models of induced seizure inhibition are 0.20 and 0.66, respectively, for 4-hydroxyalprazolam and α-hydroxyalprazolam. Such low concentrations and the lesser potencies of 4-hydroxyalprazolam and α-hydroxyalprazolam suggest that they are unlikely to contribute much to the pharmacological effects of alprazolam. The benzophenone metabolite is essentially inactive.

Alprazolam and its metabolites are excreted primarily in the urine.

Special Populations

Changes in the absorption, distribution, metabolism and excretion of benzodiazepines have been reported in a variety of disease states including alcoholism, impaired hepatic function and impaired renal function. Changes have also been demonstrated in geriatric patients. A mean half-life of alprazolam of 16.3 hours has been observed in healthy elderly subjects (range: 9.0 to 26.9 hours, n=16) compared to 11.0 hours (range: 6.3 to 15.8 hours, n=16) in healthy adult subjects. In patients with alcoholic liver disease, the half-life of alprazolam ranged between 5.8 and 65.3 hours (mean: 19.7 hours, n=17) as compared to between 6.3 and 26.9 hours (mean=11.4 hours, n=17) in healthy subjects. In an obese group of subjects, the half-life of alprazolam ranged between 9.9 and 40.4 hours (mean=21.8 hours, n=12) as compared to between 6.3 and 15.8 hours (mean=10.6 hours, n=12) in healthy subjects.

Because of its similarity to other benzodiazepines, it is assumed that alprazolam undergoes transplacental passage and that it is excreted in human milk.

Race — Maximal concentrations (Cmax) and half-life of alprazolam are approximately 15% and 25% higher in Asians compared to Caucasians.

Pediatrics — The pharmacokinetics of alprazolam in pediatric patients have not been studied.

Gender — Gender has no effect on the pharmacokinetics of alprazolam.

Cigarette Smoking — Alprazolam concentrations may be reduced by up to 50% in smokers compared to non-smokers.

Drug-Drug Interactions

Alprazolam is primarily eliminated by metabolism via cytochrome P450 3A (CYP3A). Most of the interactions that have been documented with alprazolam are with drugs that inhibit or induce CYP3A.

Compounds that are potent inhibitors of CYP3A would be expected to increase plasma alprazolam concentrations. Drug products that have been studied in vivo, along with their effect on increasing alprazolam AUC, are as follows: ketoconazole, 3.98 fold; itraconazole, 2.70 fold; nefazodone, 1.98 fold; fluvoxamine, 1.96 fold; and erythromycin, 1.61 fold [see Contraindications (4), Warnings and Precautions (5.8), and Drug Interactions (7)].

CYP3A inducers would be expected to decrease alprazolam concentrations and this has been observed in vivo. The oral clearance of alprazolam (given in a 0.8 mg single dose) was increased from 0.90 ± 0.21 mL/min/kg to 2.13 ± 0.54 mL/min/kg and the elimination t1/2 was shortened (from 17.1 ± 4.9 to 7.7 ± 1.7 h) following administration of 300 mg/day carbamazepine for 10 days [see Drug Interactions (7)]. However, the carbamazepine dose used in this study was fairly low compared to the recommended doses (1000 mg to 1200 mg/day); the effect at usual carbamazepine doses is unknown.

The ability of alprazolam to induce or inhibit human hepatic enzyme systems has not been determined. However, this is not a property of benzodiazepines in general. Further, alprazolam did not affect the prothrombin or plasma warfarin levels in male volunteers administered sodium warfarin orally.

NONCLINICAL TOXICOLOGY

13.1 Carcinogenesis, Mutagenesis, and Impairment of Fertility

No evidence of carcinogenic potential was observed during 2-year bioassay studies of alprazolam in rats at doses up to 30 mg/kg per day (30 times the maximum recommended human dose of 10 mg per day on a mg/m2 basis) and in mice at doses up to 10 mg/kg per day (5 times the maximum recommended human dose on a mg/m2).

Alprazolam also was not mutagenic in vitro in the DNA Damage/Alkaline Elution Assay or the Ames Assay, and was negative in the rat micronucleus test.

Alprazolam produced no impairment of fertility in rats at doses up to 5 mg/kg per day, which is 5 times the maximum recommended human dose of 10 mg per day on a mg/m2 basis.

13.2 Animal Toxicology and/or Pharmacology

When rats were treated with oral alprazolam doses of 3, 10, and 30 mg/kg per day (3 to 30 times the maximum recommended human dose of 10 mg per day on a mg/m2 basis) for 2 years, a tendency for a dose related increase in the number of cataracts was observed in females, and a tendency for a dose related increase in corneal vascularization was observed in males. These lesions did not appear until after 11 months of treatment.

CLINICAL STUDIES

14.1 Anxiety Disorders

The efficacy of alprazolam in the treatment of anxiety symptoms was demonstrated in five short-term (4 weeks), randomized, double-blind, placebo-controlled studies. The studies included patients with a diagnosis of anxiety or anxiety with associated depressive symptomatology. Alprazolam doses ranged from 0.5 to 4 mg per day. The mean daily doses ranged from 1.6 to 2.4 mg. Treatment with alprazolam was statistically significantly superior to placebo treatment, as measured by the following psychometric instruments: Hamilton Anxiety Rating Scale, Physician’s Global Impressions, Target Symptoms, Patient’s Global Impressions and Self-Rating Symptom Scale.

14.2 Panic Disorder

The efficacy of alprazolam in the treatment of panic disorder was demonstrated in three short-term (up to 10 weeks), randomized, double-blind, placebo-controlled studies. Patients in the studies had diagnoses corresponding closely to DSM-III-R criteria for panic disorder (with or without agoraphobia).

The average dose of alprazolam was 5 mg to 6 mg per day in two of the studies, and the doses of alprazolam were fixed at 2 mg and 6 mg per day in the third study. In all three studies, alprazolam was superior to placebo on a variable defined as "the number of patients with zero panic attacks" (range, 37 to 83% met this criterion), as well as on a global improvement score. In two of the three studies, alprazolam was superior to placebo on a variable defined as "change from baseline on the number of panic attacks per week" (range, 3.3 to 5.2), and also on a phobia rating scale. A subgroup of patients who were improved on alprazolam during short-term treatment in one of these trials was continued on an open basis up to 8 months, without apparent loss of benefit.

HOW SUPPLIED

Alprazolam orally disintegrating tablets, USP 0.25 mg are white to off-white, round, scored, flat face, beveled edge tablets debossed ‘110’ on the scored side and plain on the other. They are supplied as follows:

Blisters of 10 x 10 NDC 49884-110-74

Alprazolam orally disintegrating tablets, USP 0.5 mg are white to off-white, round, scored, flat face, beveled edge tablets debossed ‘111’ on the scored side and plain on the other. They are supplied as follows:

Blisters of 2 NDC 72189-637-02

Alprazolam orally disintegrating tablets, USP 1 mg are white to off-white, round, scored, flat face, beveled edge tablets debossed ‘213’ on the scored side and plain on the other. They are supplied as follows:

Blisters of 10 x 10 NDC 49884-213-74

Alprazolam orally disintegrating tablets, USP 2 mg are white to off-white, round, scored, flat face, beveled edge tablets debossed ‘214’ on the scored side and plain on the other. They are supplied as follows:

Blisters of 10 x 10 NDC 49884-214-74

STORAGE AND HANDLING

Store at 20° to 25°C (68° to 77°F); excursions permitted between 15° to 30°C (59° to 86ºF) [See USP Controlled Room Temperature]. Protect from moisture.

Dispense in tight, light-resistant containers as defined in the USP.

Keep container tightly closed.

PATIENT COUNSELING INFORMATION

Advise the patient to read the FDA-approved patient labeling (Medication Guide).

Risks from Concomitant Use with Opioids

Inform patients and caregivers that potentially fatal additive effects may occur if alprazolam is used with opioids and not to use such drugs concomitantly unless supervised by a health care provider [see Warnings and Precautions (5.1), Drug Interactions (7.1)].

Abuse, Misuse, and Addiction

Inform patients that the use of Alprazolam orally disintegrating tablets, even at recommended dosages, exposes users to risks of abuse, misuse, and addiction, which can lead to overdose and death, especially when used in combination with other medications (e.g., opioid analgesics), alcohol, and/or illicit substances. Inform patients about the signs and symptoms of benzodiazepine abuse, misuse, and addiction; to seek medical help if they develop these signs and/or symptoms; and on the proper disposal of unused drug [see Warnings and Precautions (5.2) and Drug Abuse and Dependence (9.2)].

Withdrawal Reactions

Inform patients that the continued use of Alprazolam orally disintegrating tablets may lead to clinically significant physical dependence and that abrupt discontinuation or rapid dosage reduction of Alprazolam orally disintegrating tablets may precipitate acute withdrawal reactions, which can be life-threatening. Inform patients that in some cases, patients taking benzodiazepines have developed a protracted withdrawal syndrome with withdrawal symptoms lasting weeks to more than 12 months. Instruct patients that discontinuation or dosage reduction of alprazolam orally disintegrating tablets may require a slow taper [see Warnings and Precautions (5.3) and Drug Abuse and Dependence (9.3)].

Use/Handling Alprazolam Orally Disintegrating Tablets

To assure safe and effective use of benzodiazepines, all patients prescribed alprazolam orally disintegrating tablets should be provided with the following guidance.

Do not remove Alprazolam orally disintegrating tablets from the blister until just prior to dosing. With dry hands, open the blister, remove the tablet, and immediately place on the tongue to dissolve and be swallowed with the saliva. The tablet may also be taken with water.
Store at room temperature in a dry place. Protect from moisture.
Inform your physician about any alcohol consumption and medicine you are taking now, including medication you may buy without a prescription. Alcohol should generally not be used during treatment with benzodiazepines.
Alprazolam orally disintegrating tablets are not recommended for use in pregnancy. Therefore, inform your physician if you are pregnant, if you are planning to have a child, or if you become pregnant while you are taking this medication.
Inform your physician if you are nursing.
Until you experience how this medication affects you, do not drive a car or operate potentially dangerous machinery, etc.
Do not increase the dose even if you think the medication “does not work anymore” without consulting your physician. Benzodiazepines, even after relatively short-term use at the doses recommended, may produce emotional and/or physical dependence.
Do not stop taking this medication abruptly or decrease the dose without consulting your physician, since withdrawal symptoms can occur even after relatively short-term use at the doses recommended. You should follow a gradual dosage tapering schedule.
Pregnancy: Advise pregnant females that use of Alprazolam orally disintegrating tablets late in pregnancy can result in sedation, (respiratory depression, withdrawal symptoms, lethargy, hypotonia) and/or withdrawal symptoms (hyperreflexia, irritability, restlessness, tremors, inconsolable crying, and feeding difficulties) in newborns [see Warnings and Precautions (5.8), Use in Specific Populations (8.1)]. Instruct patients to inform their healthcare provider if they are pregnant.

Advise patients that there is a pregnancy exposure registry that monitors pregnancy outcomes in women exposed to Alprazolam orally disintegrating tablets during pregnancy [see Use in Specific Populations (8.1)].

10. Phenylketonurics: Phenylketonuric patients should be informed that alprazolam orally disintegrating tablets contain phenylalanine (a component of aspartame). Each 0.25 mg, 0.5 mg, 1 mg and 2 mg orally disintegrating tablet contains 2.52 mg, 5.04 mg, 5.04 mg and 10.08 mg of phenylalanine, respectively [see Description (11.1)].

11. Lactation: Advise patients that breastfeeding is not recommended during treatment with Alprazolam orally disintegrating tablets [see Use in Specific Populations (8.2)].

Dispense with Medication Guide available at: www.endo.com.

Manufactured for:

Endo USA

Malvern, PA 19355 U.S.A.

Made in India

Neutral Code: TN/DRUGS/TN00002121

© 2024 Endo, Inc. or one of its affiliates.

OS110C-01-74-02

Revised: 09/2024

MEDICATION GUIDE

Alprazolam (al pra′ zoe lam)

Orally Disintegrating Tablet (ODT), C-IV

What is the most important information I should know about alprazolam ODT?

Alprazolam ODT is a benzodiazepine medicine. Taking benzodiazepines with opioid medicines, alcohol, or other central nervous system (CNS) depressants (including street drugs) can cause severe drowsiness, breathing problems (respiratory depression), coma and death. Get emergency help right away if any of the following happens:

Do not drive or operate heavy machinery until you know how taking alprazolam ODT with opioids affects you.

shallow or slowed breathing
breathing stops (which may lead to the heart stopping)
excessive sleepiness (sedation)
Risk of abuse, misuse, and addiction. There is a risk of abuse, misuse, and addiction with benzodiazepines, including alprazolam ODT which can lead to overdose and serious side effects including coma and death.

Serious side effects including coma and death have happened in people who have abused or misused benzodiazepines, including Alprazolam ODT. These serious side effects may also include delirium, paranoia, suicidal thoughts or actions, seizures, and difficulty breathing. Call your healthcare provider or go to the nearest hospital emergency room right away if you get any of these serious side effects.
You can develop an addiction even if you take Alprazolam ODT exactly as prescribed by your healthcare provider.

Take Alprazolam ODT exactly as your healthcare provider prescribed.
Do not share your Alprazolam ODT with other people.
Keep Alprazolam ODT in a safe place and away from children.

Physical dependence and withdrawal reactions. Alprazolam ODT can cause physical dependence and withdrawal reactions, especially if you continue to take Alprazolam ODT for several days to several weeks.

Do not suddenly stop taking Alprazolam ODT. Stopping Alprazolam ODT suddenly can cause serious and life-threatening side effects, including, unusual movements, responses, or expressions, seizures, sudden and severe mental or nervous system changes, depression, seeing or hearing things that others do not see or hear, an extreme increase in activity or talking, losing touch with reality, and suicidal thoughts or actions. Call your healthcare provider or go to the nearest hospital emergency room right away if you get any of these symptoms.
Some people who suddenly stop benzodiazepines have symptoms that can last for several weeks to more than 12 months, including, anxiety, trouble remembering, learning, or concentrating, depression, problems sleeping, feeling like insects are crawling under your skin, weakness, shaking, muscle twitching, burning or prickling feeling in your hands, arms, legs or feet, and ringing in your ears.
Physical dependence is not the same as drug addiction. Your healthcare provider can tell you more about the differences between physical dependence and drug addiction.
Do not take more Alprazolam ODT than prescribed or take Alprazolam ODT for longer than prescribed.

What is alprazolam ODT?

Alprazolam ODT is a prescription medicines used to treat:

generalized anxiety disorder
panic disorder with or without fear of places and situations that might cause panic, helplessness, or embarrassment (agoraphobia)

Alprazolam ODT is a federal controlled substance (C-IV) because it contains alprazolam that can be abused or lead to dependence. Keep alprazolam ODT in a safe place to prevent misuse and abuse. Selling or giving away alprazolam ODT may harm others, and is against the law. Tell your healthcare provider if you have abused or been dependent on alcohol, prescription medicines or street drugs.
It is not known if alprazolam ODT is safe and effective in children.
It is not known if alprazolam ODT is safe and effective when to treat generalized anxiety disorder for longer than 4 months.
It is not known if alprazolam ODT is safe and effective when used to treat panic disorder for longer than 10 weeks.

Do not take alprazolam ODT if you:

take an antifungal medicines including ketoconazole and itraconazole

Before you take alprazolam ODT, tell your healthcare provider about all your medical conditions, including if you:

have or have had depression, mood problems, or suicidal thoughts or behavior
have liver or kidney problems
have lung disease or breathing problems
are pregnant or plan to become pregnant. You and your healthcare provider should decide if you should take alprazolam ODT while you are pregnant.

Taking alprazolam ODT late in pregnancy may cause your baby to have symptoms of sedation (breathing problems, sluggishness, low muscle tone), and/or withdrawal symptoms (jitteriness, irritability, restlessness, shaking, excessive crying, feeding problems).
Tell your healthcare provider right away if you become pregnant or think you are pregnant during treatment with alprazolam ODT.
There is a pregnancy registry for women who take alprazolam ODT during pregnancy. The purpose of the registry is to collect information about the health of you and your baby. If you become pregnant during treatment with alprazolam ODT, talk to your healthcare provider about registering with the National Pregnancy Registry for Psychiatric Medications. You can register by calling 1-866-961-2388 or visiting https://womensmentalhealth.org/research/pregnancyregistry/.

are breastfeeding or plan to breastfeed. Alprazolam passes into your breast milk

Talk to your healthcare provider about the best way to feed your baby if you take alprazolam ODT.
Breastfeeding is not recommended during treatment with alprazolam ODT.

Tell your healthcare provider about all the medicines you take, including prescription and over-the-counter medicines, vitamins, and herbal supplements.

Taking alprazolam ODT with certain other medicines can cause side effects or affect how well alprazolam ODT or the other medicines work. Do not start or stop other medicines without talking to your healthcare provider.

How should I take alprazolam ODT?

Take alprazolam ODT exactly as your healthcare provider tells you to take it. Your healthcare provider will tell you how much alprazolam ODT to take and when to take it.
Do not remove alprazolam ODT from the blister until you are ready to take it. With dry hands, remove the alprazolam ODT, and immediately place on your tongue to dissolve and be swallowed with your saliva. The tablet may also be taken with water.
If you take too much alprazolam ODT, call your healthcare provider or go to the nearest hospital emergency room right away.

What are the possible side effects of alprazolam ODT?

Alprazolam ODT may cause serious side effects, including:

See “What is the most important information I should know about alprazolam ODT?”
Seizures. Stopping alprazolam ODT can cause seizures and seizures that will not stop (status epilepticus).
Mania. Alprazolam ODT may cause an increase in activity and talking (hypomania and mania) in people who have depression.
Alprazolam ODT can make you sleepy or dizzy and can slow your thinking and motor skills.

Do not drive, operate heavy machinery, or do other dangerous activities until you know how Alprazolam ODT affects you.
Do not drink alcohol or take other medicines that may make you sleepy or dizzy while taking Alprazolam ODT without first talking to your healthcare provider. When taken with alcohol or other medicines that cause sleepiness or dizziness, Alprazolam ODT may make your sleepiness or dizziness much worse.

The most common side effects of alprazolam ODT include:

sedation
problems with coordination
speech problems (dysarthria)
increased libido
low blood pressure (hypotension)

These are not all the possible side effects of alprazolam ODT. Call your doctor for medical advice about side effects. You may report side effects to FDA at 1-800-FDA-1088.

How should I store alprazolam ODT?

Store alprazolam ODT at room temperature between 68°F to 77°F (20°C to 25°C).
Keep alprazolam ODT in a tightly closed container and keep dry.
Keep alprazolam ODT and all medicines out of the reach of children.

General information about the safe and effective use of alprazolam ODT.

Medicines are sometimes prescribed for purposes other than those listed in a Medication Guide. Do not use alprazolam ODT for a condition for which it was not prescribed. Do not give alprazolam ODT to other people, even if they have the same symptoms that you have. It may harm them. You can ask your pharmacist or healthcare provider for information about alprazolam ODT that is written for health professionals. For more information call 1-800-828-9393.

What are the ingredients in alprazolam ODT?

Active ingredients: alprazolam

Inactive ingredients: aspartame, crospovidone, basic butylated methacrylate copolymer, magnesium stearate, mannitol, silicon dioxide, sorbitol, talc, xylitol, natural peppermint flavor, artificial vanillin flavor.

Manufactured for:

Endo USA

Malvern, PA 19355 U.S.A.

Made in India

Neutral Code: TN/DRUGS/TN00002121

© 2024 Endo, Inc. or one of its affiliates.

OS110C-01-74-02

Revised: 09/2024

This Medication Guide has been approved by the U.S. Food and Drug Administration